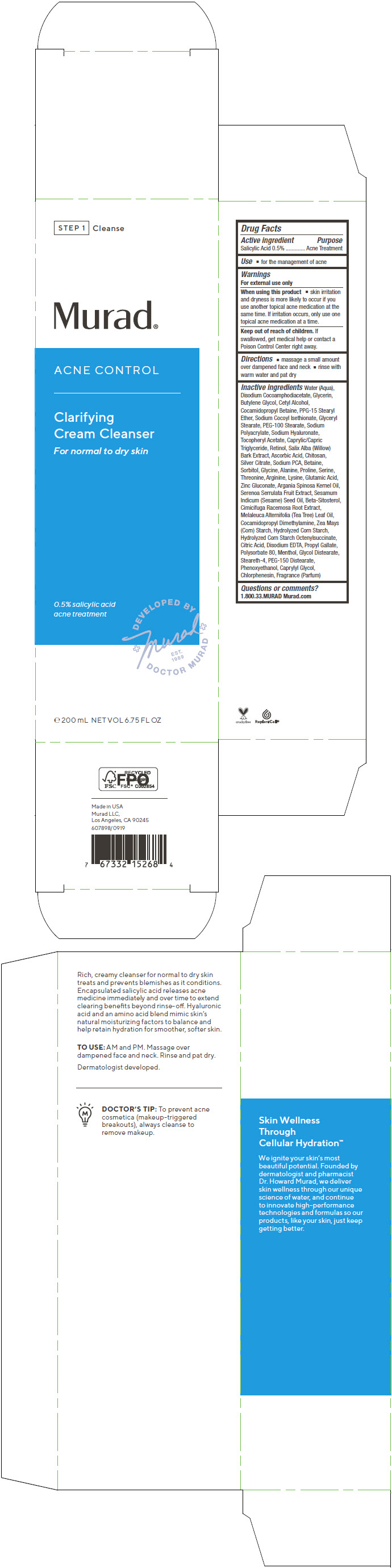 DRUG LABEL: Acne Control Clarifying Cream Cleanser
NDC: 70381-114 | Form: CREAM
Manufacturer: Murad, LLC
Category: otc | Type: HUMAN OTC DRUG LABEL
Date: 20210702

ACTIVE INGREDIENTS: SALICYLIC ACID 0.5 g/100 mL
INACTIVE INGREDIENTS: WATER; DISODIUM COCOAMPHODIACETATE; GLYCERIN; BUTYLENE GLYCOL; CETYL ALCOHOL; COCAMIDOPROPYL BETAINE; PPG-15 STEARYL ETHER; SODIUM COCOYL ISETHIONATE; GLYCERYL MONOSTEARATE; PEG-100 STEARATE; SODIUM POLYACRYLATE (2500000 MW); HYALURONATE SODIUM; .ALPHA.-TOCOPHEROL ACETATE; MEDIUM-CHAIN TRIGLYCERIDES; RETINOL; SALIX ALBA BARK; ASCORBIC ACID; POLIGLUSAM; SILVER CITRATE; SODIUM PYRROLIDONE CARBOXYLATE; BETAINE; SORBITOL; GLYCINE; ALANINE; PROLINE; SERINE; THREONINE; ARGININE; LYSINE; GLUTAMIC ACID; ZINC GLUCONATE; ARGAN OIL; SAW PALMETTO; SESAME OIL; .BETA.-SITOSTEROL; BLACK COHOSH; TEA TREE OIL; COCAMIDOPROPYL DIMETHYLAMINE; STARCH, CORN; CORN SYRUP; CITRIC ACID MONOHYDRATE; EDETATE DISODIUM ANHYDROUS; PROPYL GALLATE; POLYSORBATE 80; MENTHOL, UNSPECIFIED FORM; GLYCOL DISTEARATE; STEARETH-4; PEG-150 DISTEARATE; PHENOXYETHANOL; CAPRYLYL GLYCOL; CHLORPHENESIN

Acne Control Clarifying Cream Cleanser

Drug Facts

Active ingredient

Salicylic Acid 0.5%

Purpose

Acne Treatment

Use

- for the management of acne

Warnings

For external use only

When using this product

- skin irritation and dryness is more likely to occur if you use another topical acne medication at the same time. If irritation occurs, only use one topical acne medication at a time.

Keep out of reach of children. If swallowed, get medical help or contact a Poison Control Center right away.

Directions

- massage a small amount over dampened face and neck
- rinse with warm water and pat dry

Inactive ingredients

Water (Aqua), Disodium Cocoamphodiacetate, Glycerin, Butylene Glycol, Cetyl Alcohol, Cocamidopropyl Betaine, PPG-15 Stearyl Ether, Sodium Cocoyl Isethionate, Glyceryl Stearate, PEG-100 Stearate, Sodium Polyacrylate, Sodium Hyaluronate, Tocopheryl Acetate, Caprylic/Capric Triglyceride, Retinol, Salix Alba (Willow) Bark Extract, Ascorbic Acid, Chitosan, Silver Citrate, Sodium PCA, Betaine, Sorbitol, Glycine, Alanine, Proline, Serine, Threonine, Arginine, Lysine, Glutamic Acid, Zinc Gluconate, Argania Spinosa Kernel Oil, Serenoa Serrulata Fruit Extract, Sesamum Indicum (Sesame) Seed Oil, Beta-Sitosterol, Cimicifuga Racemosa Root Extract, Melaleuca Alternifolia (Tea Tree) Leaf Oil, Cocamidopropyl Dimethylamine, Zea Mays (Corn) Starch, Hydrolyzed Corn Starch, Hydrolyzed Corn Starch Octenylsuccinate, Citric Acid, Disodium EDTA, Propyl Gallate, Polysorbate 80, Menthol, Glycol Distearate, Steareth-4, PEG-150 Distearate, Phenoxyethanol, Caprylyl Glycol, Chlorphenesin, Fragrance (Parfum)

Questions or comments?

1.800.33.MURAD Murad.com

PRINCIPAL DISPLAY PANEL - 200 mL Tube Carton

STEP 1 Cleanse

Murad®

ACNE CONTROL

Clarifying
Cream Cleanser

For normal to dry skin

0.5% salicylic acid
acne treatment

DEVELOPED BY
Murad
EST.
1989
DOCTOR MURAD

e 200 mL NET VOL 6.75 FL OZ